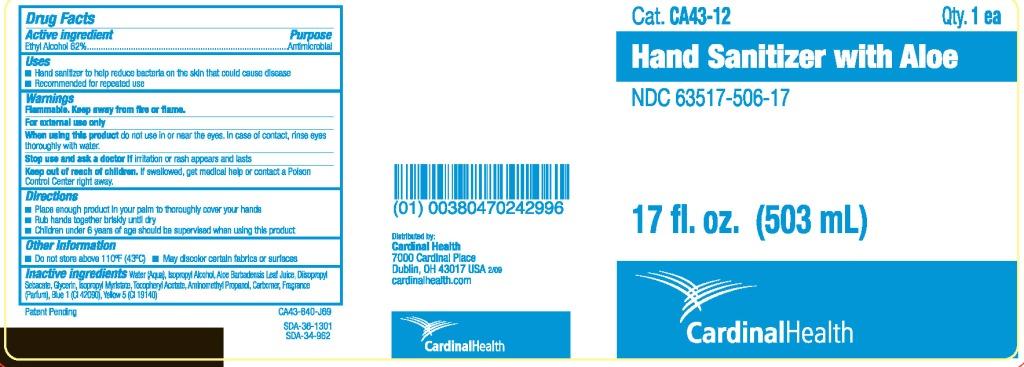 DRUG LABEL: Cardinal Health Hand Sanitizer with Aloe
NDC: 63517-506 | Form: GEL
Manufacturer: Cardinal Health
Category: otc | Type: HUMAN OTC DRUG LABEL
Date: 20110302

ACTIVE INGREDIENTS: ALCOHOL 0.62 mL/1 mL
INACTIVE INGREDIENTS: WATER; ISOPROPYL ALCOHOL; ALOE VERA LEAF

PACKAGE LABEL

Cardinal Health Hand Sanitizer with Aloe

Directions

- Place enough product in your palm to thoroughly cover your hands
- Rub hands together briskly until dry
- Children under 6 years of age should be supervised when using this product

DOSAGE AND ADMINISTRATION

Apply approx. 1.5 mL

PURPOSE

Antimicrobial

Keep out of reach of children.

Warnings
For external use only
When using this product do not use in or near the eyes. In case of contact, rinse eyes thoroughly with water.
Stop use and ask a doctor if irritation or rash appears and lasts
Keep out of reach of children. If swallowed, get medical help or contact a Poison Control Center right away.

Active ingredient Ethyl alcohol 62%

INACTIVE INGREDIENT

Inactive ingredients Water (Aqua), Isopropyl Alcohol, Aloe Barbadensis Leaf Juice, Diisopropyl Sebacate, Glycerin, Isopropyl Myristate, Tocopheryl Acetate, Aminomethyl Propanol, Carbomer, Fragrance (Parfum), Blue 1 (CI 42090), Yellow 5 (CI 19140)